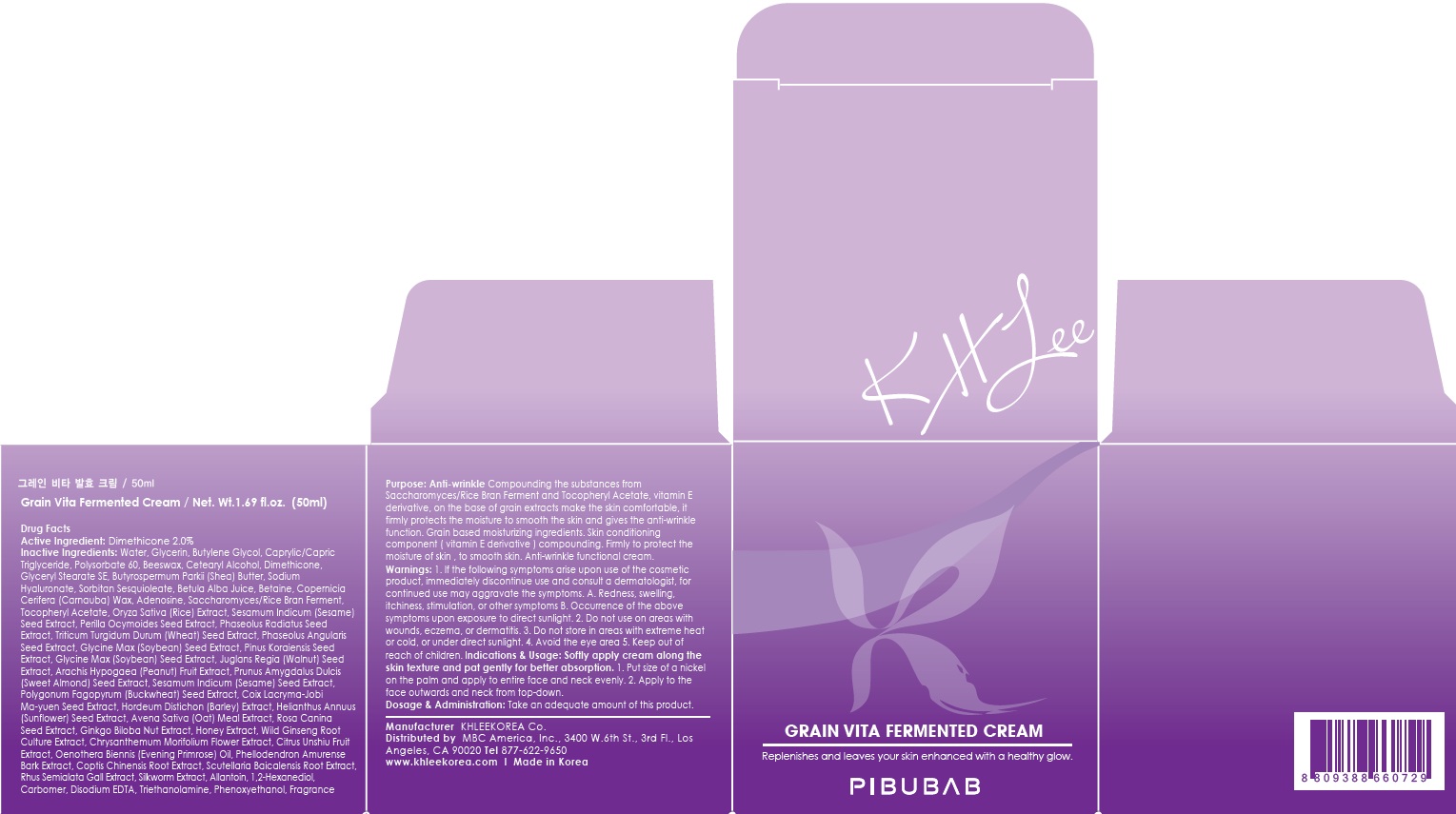 DRUG LABEL: Grain Vita Fermented
NDC: 70567-040 | Form: CREAM
Manufacturer: KHLEEKOREA
Category: otc | Type: HUMAN OTC DRUG LABEL
Date: 20160418

ACTIVE INGREDIENTS: Dimethicone 1.0 g/50 mL
INACTIVE INGREDIENTS: Water; Glycerin

ACTIVE INGREDIENT

Active Ingredient: Dimethicone 2.0%

INACTIVE INGREDIENT

Inactive Ingredients: Water, Glycerin, Butylene Glycol, Caprylic/Capric Triglyceride, Polysorbate 60, Beeswax, Cetearyl Alcohol, Glyceryl Stearate SE, Butyrospermum Parkii (Shea) Butter, Sodium Hyaluronate, Sorbitan Sesquioleate, Betula Alba Juice, Betaine, Copernicia Cerifera (Carnauba) Wax, Adenosine, Saccharomyces/Rice Bran Ferment, Tocopheryl Acetate, Oryza Sativa (Rice) Extract, Sesamum Indicum (Sesame) Seed Extract, Perilla Ocymoides Seed Extract, Phaseolus Radiatus Seed Extract, Triticum Turgidum Durum (Wheat) Seed Extract, Phaseolus Angularis Seed Extract, Glycine Max (Soybean) Seed Extract, Pinus Koraiensis Seed Extract, Glycine Max (Soybean) Seed Extract, Juglans Regia (Walnut) Seed Extract, Arachis Hypogaea (Peanut) Fruit Extract, Prunus Amygdalus Dulcis (Sweet Almond) Seed Extract, Sesamum Indicum (Sesame) Seed Extract, Polygonum Fagopyrum (Buckwheat) Seed Extract, Coix Lacryma-Jobi Ma-yuen Seed Extract, Hordeum Distichon (Barley) Extract, Helianthus Annuus (Sunflower) Seed Extract, Avena Sativa (Oat) Meal Extract, Rosa Canina Seed Extract, Ginkgo Biloba Nut Extract, Honey Extract, Wild Ginseng Root Culture Extract, Chrysanthemum Morifolium Flower Extract, Citrus Unshiu Fruit Extract, Oenothera Biennis (Evening Primrose) Oil, Phellodendron Amurense Bark Extract, Coptis Chinensis Root Extract, Scutellaria Baicalensis Root Extract, Rhus Semialata Gall Extract, Silkworm Extract, Allantoin, 1,2-Hexanediol, Carbomer, Disodium EDTA, Triethanolamine, Phenoxyethanol, Fragrance

PURPOSE

Purpose: Anti-wrinkle

Compounding the substances from Saccharomyces/Rice Bran Ferment and Tocopheryl Acetate, vitamin E derivative, on the base of grain extracts make the skin comfortable, it firmly protects the moisture to smooth the skin and gives the anti-wrinkle function. Grain based moisturizing ingredients. Skin conditioning component (vitamin E derivative) compounding. Firmly to protect the moisture of skin , to smooth skin. Anti-wrinkle functional cream.

WARNINGS

Warnings: 1. If the following symptoms arise upon use of the cosmetic product, immediately discontinue use and consult a dermatologist, for continued use may aggravate the symptoms. A. Redness, swelling, itchiness, stimulation, or other symptoms B. Occurrence of the above symptoms upon exposure to direct sunlight. 2. Do not use on areas with wounds, eczema, or dermatitis. 3. Do not store in areas with extreme heat or cold, or under direct sunlight. 4. Avoid the eye area 5. Keep out of reach of children

KEEP OUT OF REACH OF CHILDREN

INDICATIONS & USAGE

Indications & Usage: Softly apply cream along the skin texture and pat gently for better absorption. 1. Put size of a nickel on the palm and apply to entire face and neck evenly. 2. Apply to the face outwards and neck from tap-down.

DOSAGE & ADMINISTRATION

Dosage & Administration: Take an adequate amount of this product.